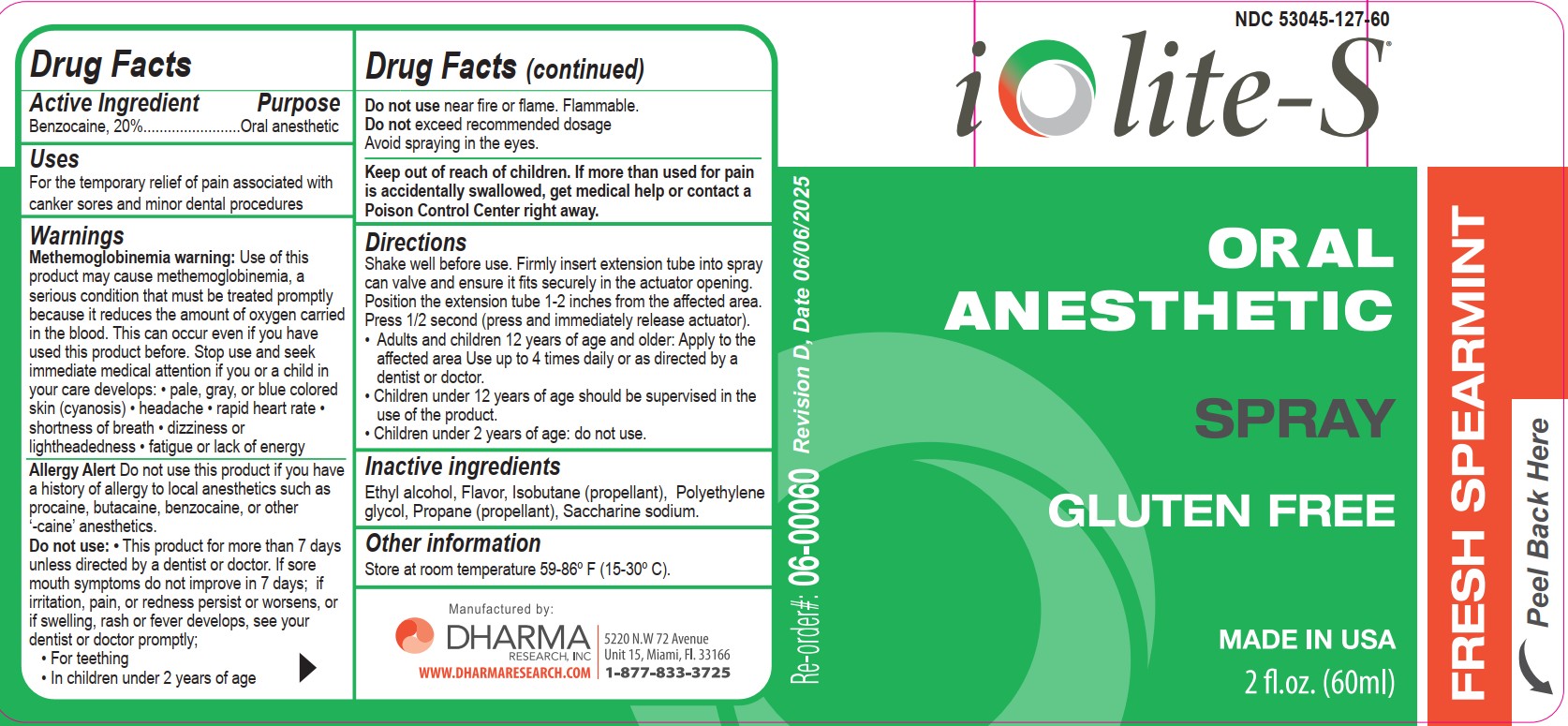 DRUG LABEL: Iolite-S
NDC: 53045-127 | Form: SPRAY
Manufacturer: Dharma Research, Inc.
Category: otc | Type: HUMAN OTC DRUG LABEL
Date: 20250614

ACTIVE INGREDIENTS: BENZOCAINE 12 g/100 mL
INACTIVE INGREDIENTS: ALCOHOL; ISOBUTANE; POLYETHYLENE GLYCOL 400; PROPANE; SACCHARIN SODIUM

Active Ingredient

Benzocaine 20%

Purpose

Oral anesthetic

Uses

For the temporary relief of occasional minor irritation and pain associated with canker sores and minor dental procedures.

Warnings

Methemoglobinemia Warning

Use of this product may cause methemoglobinemia, a serious condition that must be treated promptly because it reduces the amount of oxygen carried in the blood. This can occur even if you have use this product before.

Stop use and seek immediate medical attention if you or a child in your care develops:

- pale, gray, or blue colored skin (cyanosis)
- headache
- rapid heart rate
- shortness of breath
- dizziness or lightheadedness
- fatigue or lack of energy

Allergy Alert

Do not use this product if you have a history of allergy to local anesthetics such as procaine, butacaine, benzocaine, or other '-caine' anesthetics.

Do not use this product for more than 7 days unless directed by a dentist or doctor. If sore mouth symptoms do not improve in 7 days; if irritation, pain, or redness persist or worsens, or if swelling, rash, or fever develops, see your dentist or doctor promptly.

- For teething
- In children under 2 years of age

Do not use near fire or flame. Flammable.

Do not exceed recommended dosage.

Avoid spraying in the eyes.

Keep out of reach of children. If more than used for pain is accidentially swallowed, get medical help or contact a Poison Control Center right away.

Directions

Shake well before use. Firmly insert extension tube into spray can valve and ensure it fits securely in the actuator opening. Position the extension tube 1-2 inches from the affected area. Press 1/2 second (press and immediately release the actuator).

- Adults and children 12 years of age and older: Apply to the affected area. Use up to 4 times daily or as directed by a dentist or doctor.
- Children under 12 years of age should be supervised in the use of this product.
- Children under 2 years of age: do not use.

Inactive Ingredients

Ethyl alcohol, Flavor, Isobutane (propellant), Polyethylene glycol, Propane (propellant), Saccharine sodium.

Other Information

Store at room temperature 59-86°F (15-30°C).

Manufactured by:

Dharma Research, Inc.

www.dharmaresearch.com

5220 N.W. 72 Avenue, Unit 15

Miami, FL 33166

1-877-833-3725

NDC 53045-127-60

Iolite-S

Oral Anesthetic Spray

Gluten Free

Made in USA

2 fl. oz. (60 mL)

Fresh Spearmint